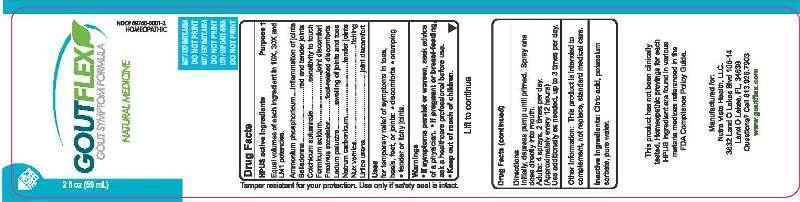 DRUG LABEL: GoutFlex Gout Symptom Formula
NDC: 69760-0001 | Form: LIQUID
Manufacturer: Nutra Vista Health LLC.
Category: homeopathic | Type: HUMAN OTC DRUG LABEL
Date: 20150929

ACTIVE INGREDIENTS: AMMONIUM PHOSPHATE, DIBASIC 10 [hp_X]/59 mL; ATROPA BELLADONNA 10 [hp_X]/59 mL; COLCHICUM AUTUMNALE BULB 10 [hp_X]/59 mL; FORMIC ACID 10 [hp_X]/59 mL; FRAXINUS EXCELSIOR BARK 10 [hp_X]/59 mL; FRAXINUS EXCELSIOR LEAF 10 [hp_X]/59 mL; LEDUM PALUSTRE TWIG 10 [hp_X]/59 mL; SODIUM CARBONATE 10 [hp_X]/59 mL; STRYCHNOS NUX-VOMICA SEED 10 [hp_X]/59 mL; URTICA URENS 10 [hp_X]/59 mL
INACTIVE INGREDIENTS: ANHYDROUS CITRIC ACID; POTASSIUM SORBATE; WATER

GoutFlex Gout Symptom Formula

ACTIVE INGREDIENT

Drug Facts__________________________________________________________________________________________________________

HPUS active ingredients Purpose †

Equal volumes of each ingredient in 10X, 30X and LM1 potencies.

Ammonium phosphoricum, Belladonna, Colchicum autumnale, Formicum acidum, Fraxinus excelsior, Ledum palustre, Natrum carbonicum, Nux vomica, Urtica urens.

INDICATIONS AND USAGE

Uses for temporary relief of symptoms in toes, heels, feet, or joints: • discomforts • cramping • tender or itchy joints.

Warnings

- If symptoms persist or worsen, seek advice of a physician.
- If pregnant or breast-feeding, ask a healthcare professional before use.

- Keep out of reach of children.

Directions

Initially, depress pump until primed. Spray one dose directly into mouth. Adults: 4 sprays 2 times per day. (approximately every 12 hours) Use additionally as needed, up to 3 times per day.

Other Information: This product is intended to complement, not replace, standard medical care.

This product has not been clinically tested. Homeopathic provings for each HPUS ingredient are found in various materia medicas referenced in the FDA Compliance Policy Guide.

Manufactured for: Nutra Vista Health, LLC. 3632 Land O Lakes Blvd 106-14 Land O Lakes, FL, 34639 Questions? Call 813.926.7903 www.goutflex.com

Inactive Ingredients:

Citric acid, potassium sorbate, pure water.

Drug Facts

__________________________________________________________________________________________________________

HPUS active ingredients Purpose †

Equal volumes of each ingredient in 10X, 30X and LM1 potencies.

Ammonium phosphoricum...........................inflammation of joints

Belladonna.................................................red and tender joints

Colchicum autumnale......................................sensitivity to touch

Formicum acidum...............................................joint discomfort

Fraxinus excelsior...................................foot-related discomforts

Ledum palustre...................................swelling of joints and toes

Natrum carbonicum...............................................tender joints

Nux vomica..................................................................itching

Urtica urens.....................................................joint discomfort